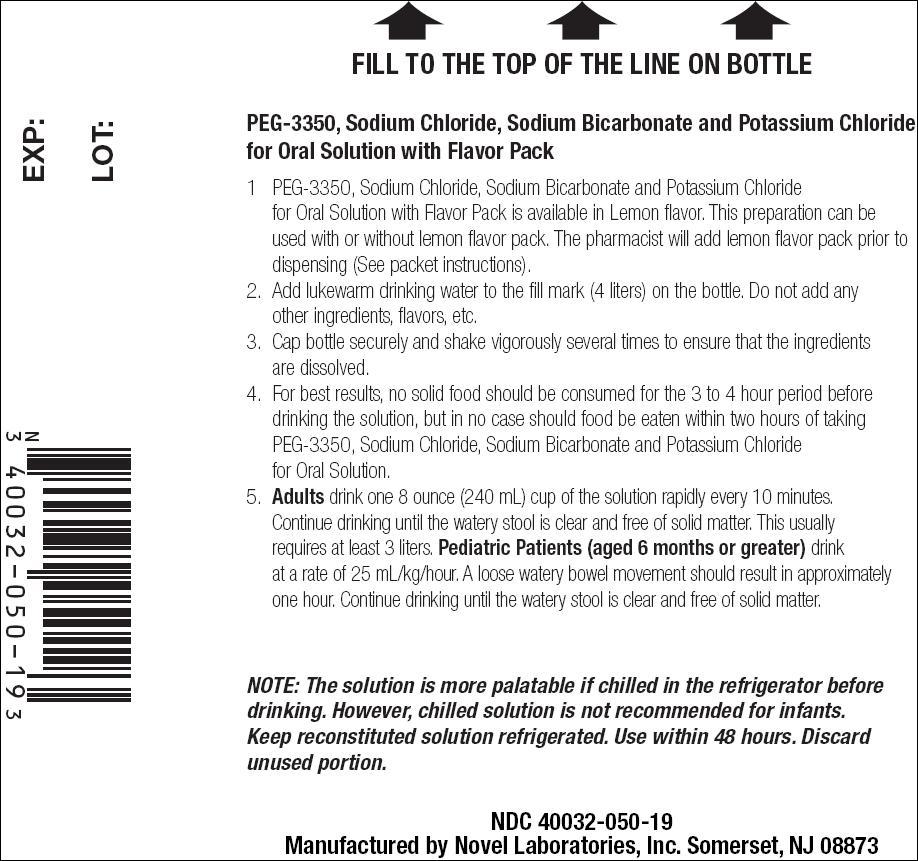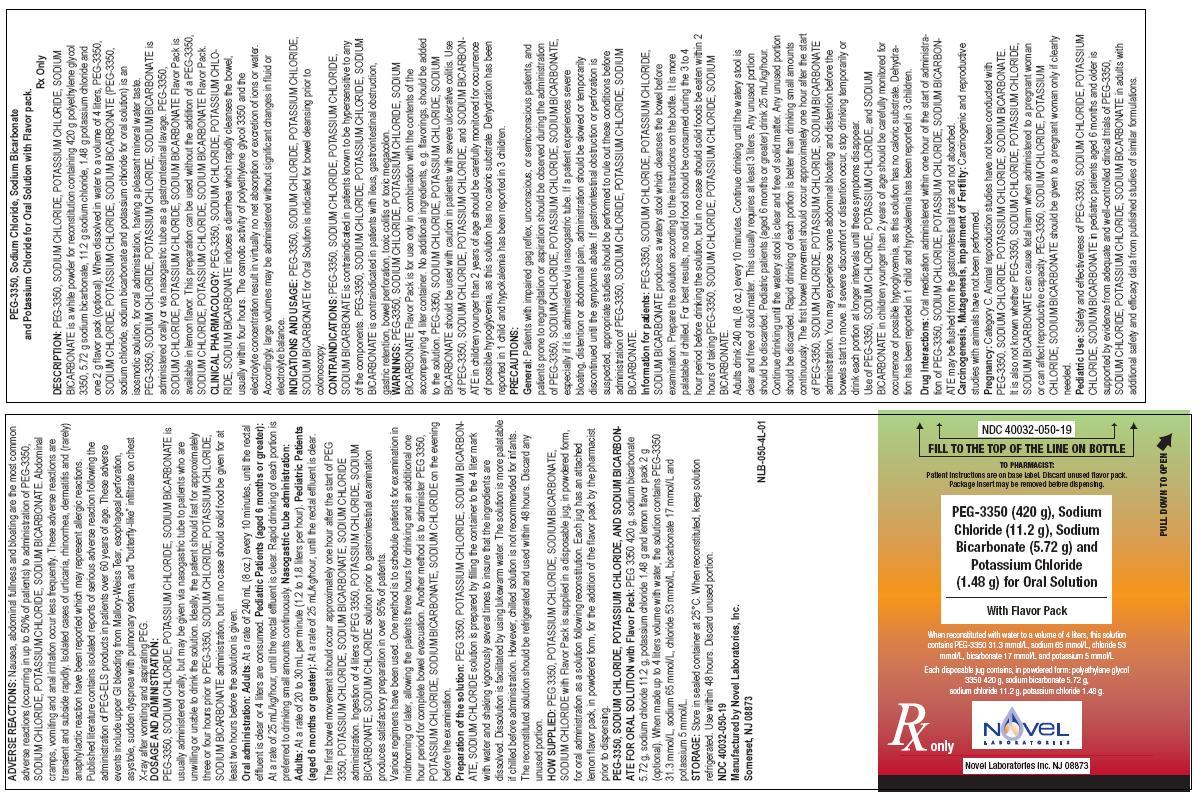 DRUG LABEL: Polyethylene Glycol-3350, Sodium Chloride, Potassium Chloride and Sodium Bicarbonate
NDC: 40032-050 | Form: POWDER, FOR SOLUTION
Manufacturer: Novel Laboratories, Inc.
Category: prescription | Type: HUMAN PRESCRIPTION DRUG LABEL
Date: 20090528

ACTIVE INGREDIENTS: POLYETHYLENE GLYCOL 3350 420 g/438.4 g; SODIUM CHLORIDE 11.2 g/438.4 g; SODIUM BICARBONATE 5.72 g/438.4 g; POTASSIUM CHLORIDE 1.48 g/438.4 g
INACTIVE INGREDIENTS: ALPHA-TOCOPHEROL, DL-; SACCHARIN SODIUM; MALTODEXTRIN; ACACIA

PEG-3350, Sodium Chloride, Sodium Bicarbonate and Potassium Chloride for Oral Solution with Flavor pack

Rx Only

DESCRIPTION

PEG-3350, SODIUM CHLORIDE, POTASSIUM CHLORIDE, SODIUM BICARBONATE is a white powder for reconstitution containing 420 g polyethylene glycol 3350, 5.72 g sodium bicarbonate, 11.2 g sodium chloride, 1.48 g potassium chloride and one 2 g flavor pack (optional). When dissolved in water to a volume of 4 liters, PEG-3350, SODIUM CHLORIDE, POTASSIUM CHLORIDE, SODIUM BICARBONATE (PEG-3350, sodium chloride, sodium bicarbonate and potassium chloride for oral solution) is an isosmotic solution, for oral administration, having a pleasant mineral water taste. PEG-3350, SODIUM CHLORIDE, POTASSIUM CHLORIDE, SODIUM BICARBONATE is administered orally or via nasogastric tube as a gastrointestinal lavage. PEG-3350, SODIUM CHLORIDE, POTASSIUM CHLORIDE, SODIUM BICARBONATE Flavor Pack is available in lemon flavor. This preparation can be used without the addition of a PEG-3350, SODIUM CHLORIDE, POTASSIUM CHLORIDE, SODIUM BICARBONATE Flavor Pack.

CLINICAL PHARMACOLOGY

PEG-3350, SODIUM CHLORIDE, POTASSIUM CHLORIDE, SODIUM BICARBONATE induces a diarrhea which rapidly cleanses the bowel, usually within four hours. The osmotic activity of polyethylene glycol 3350 and the electrolyte concentration result in virtually no net absorption or excretion of ions or water. Accordingly, large volumes may be administered without significant changes in fluid or electrolyte balance.

INDICATIONS AND USAGE

PEG-3350, SODIUM CHLORIDE, POTASSIUM CHLORIDE, SODIUM BICARBONATE for Oral Solution is indicated for bowel cleansing prior to colonoscopy.

CONTRAINDICATIONS

PEG-3350, SODIUM CHLORIDE, POTASSIUM CHLORIDE, SODIUM BICARBONATE is contraindicated in patients known to be hypersensitive to any of the components. PEG-3350, SODIUM CHLORIDE, POTASSIUM CHLORIDE, SODIUM BICARBONATE is contraindicated in patients with ileus, gastrointestinal obstruction, gastric retention, bowel perforation, toxic colitis or toxic megacolon.

WARNINGS

PEG-3350, SODIUM CHLORIDE, POTASSIUM CHLORIDE, SODIUM BICARBONATE Flavor Pack is for use only in combination with the contents of the accompanying 4 liter container. No additional ingredients, e.g. flavorings, should be added to the solution. PEG-3350, SODIUM CHLORIDE, POTASSIUM CHLORIDE, SODIUM BICARBONATE should be used with caution in patients with severe ulcerative colitis. Use of PEG-3350, SODIUM CHLORIDE, POTASSIUM CHLORIDE, and SODIUM BICARBONATE in children younger than 2 years of age should be carefully monitored for occurrence of possible hypoglycemia, as this solution has no caloric substrate. Dehydration has been reported in 1 child and hypokalemia has been reported in 3 children.

PRECAUTIONS

General

Patients with impaired gag reflex, unconscious, or semiconscious patients, and patients prone to regurgitation or aspiration should be observed during the administration of PEG-3350, SODIUM CHLORIDE, POTASSIUM CHLORIDE, SODIUM BICARBONATE, especially if it is administered via nasogastric tube. If a patient experiences severe bloating, distention or abdominal pain, administration should be slowed or temporarily discontinued until the symptoms abate. If gastrointestinal obstruction or perforation is suspected, appropriate studies should be performed to rule out these conditions before administration of PEG-3350, SODIUM CHLORIDE, POTASSIUM CHLORIDE, SODIUM BICARBONATE.

Information for Patients

PEG-3350, SODIUM CHLORIDE, POTASSIUM CHLORIDE, SODIUM BICARBONATE produces a watery stool which cleanses the bowel before examination. Prepare the solution according to the instructions on the bottle. It is more palatable if chilled. For best results, no solid food should be consumed during the 3 to 4 hour period before drinking the solution, but in no case should solid foods be eaten within 2 hours of taking PEG-3350, SODIUM CHLORIDE, POTASSIUM CHLORIDE, SODIUM BICARBONATE.

Adults drink 240 mL (8 oz.) every 10 minutes. Continue drinking until the watery stool is clear and free of solid matter. This usually requires at least 3 liters. Any unused portion should be discarded. Pediatric patients (aged 6 months or greater) drink 25 mL/kg/hour. Continue drinking until the watery stool is clear and free of solid matter. Any unused portion should be discarded. Rapid drinking of each portion is better than drinking small amounts continuously. The first bowel movement should occur approximately one hour after the start of PEG-3350, SODIUM CHLORIDE, POTASSIUM CHLORIDE, SODIUM BICARBONATE administration. You may experience some abdominal bloating and distention before the bowels start to move. If severe discomfort or distention occur, stop drinking temporarily or drink each portion at longer intervals until these symptoms disappear.

Use of PEG-3350, SODIUM CHLORIDE, POTASSIUM CHLORIDE, and SODIUM BICARBONATE in children younger than 2 years of age should be carefully monitored for occurrence of possible hypoglycemia, as this solution has no caloric substrate. Dehydration has been reported in 1 child and hypokalemia has been reported in 3 children.

Drug Interactions

Oral medication administered within one hour of the start of administration of PEG-3350, SODIUM CHLORIDE, POTASSIUM CHLORIDE, SODIUM BICARBONATE may be flushed from the gastrointestinal tract and not absorbed.

Carcinogenesis, Mutagenesis, Impairment of Fertility

Carcinogenic and reproductive studies with animals have not been performed.

Pregnancy

Category C. Animal reproduction studies have not been conducted with PEG-3350, SODIUM CHLORIDE, POTASSIUM CHLORIDE, SODIUM BICARBONATE. It is also not known whether PEG-3350, SODIUM CHLORIDE, POTASSIUM CHLORIDE, SODIUM BICARBONATE can cause fetal harm when administered to a pregnant woman or can affect reproductive capacity. PEG-3350, SODIUM CHLORIDE, POTASSIUM CHLORIDE, SODIUM BICARBONATE should be given to a pregnant woman only if clearly needed.

Pediatric Use

Safety and effectiveness of PEG-3350, SODIUM CHLORIDE, POTASSIUM CHLORIDE, SODIUM BICARBONATE in pediatric patients aged 6 months and older is supported by evidence from adequate and well-controlled clinical trials of PEG-3350, SODIUM CHLORIDE, POTASSIUM CHLORIDE, SODIUM BICARBONATE in adults with additional safety and efficacy data from published studies of similar formulations.

ADVERSE REACTIONS

Nausea, abdominal fullness and bloating are the most common adverse reactions (occurring in up to 50% of patients) to administration of PEG-3350, SODIUM CHLORIDE, POTASSIUM CHLORIDE, SODIUM BICARBONATE. Abdominal cramps, vomiting and anal irritation occur less frequently. These adverse reactions are transient and subside rapidly. Isolated cases of urticaria, rhinorrhea, dermatitis and (rarely) anaphylactic reaction have been reported which may represent allergic reactions. Published literature contains isolated reports of serious adverse reaction following the administration of PEG-ELS products in patients over 60 years of age. These adverse events include upper GI bleeding from Mallory-Weiss Tear, esophageal perforation, asystole, sudden dyspnea with pulmonary edema, and "butterfly-like” infiltrate on chest X-ray after vomiting and aspirating PEG.

DOSAGE AND ADMINISTRATION

PEG-3350, SODIUM CHLORIDE, POTASSIUM CHLORIDE, SODIUM BICARBONATE is usually administered orally, but may be given via nasogastric tube to patients who are unwilling or unable to drink the solution. Ideally, the patient should fast for approximately three or four hours prior to PEG-3350, SODIUM CHLORIDE, POTASSIUM CHLORIDE, SODIUM BICARBONATE administration, but in no case should solid food be given for at least two hours before the solution is given.

Oral administration

Adults: At a rate of 240 mL (8 oz.) every 10 minutes, until the rectal effluent is clear or 4 liters are consumed. Pediatric Patients (aged 6 months or greater): At a rate of 25 mL/kg/hour, until the rectal effluent is clear. Rapid drinking of each portion is preferred to drinking small amounts continuously. Nasogastric tube administration: Adults: At a rate of 20 to 30 mL per minute (1.2 to 1.8 liters per hour). Pediatric Patients (aged 6 months or greater): At a rate of 25 mL/kg/hour, until the rectal effluent is clear.

The first bowel movement should occur approximately one hour after the start of PEG-3350, POTASSIUM CHLORIDE, SODIUM BICARBONATE, SODIUM CHLORIDE administration. Ingestion of 4 liters of PEG-3350, POTASSIUM CHLORIDE, SODIUM BICARBONATE, SODIUM CHLORIDE solution prior to gastrointestinal examination produces satisfactory preparation in over 95% of patients.

Various regimens have been used. One method is to schedule patients for examination in midmorning or later, allowing the patients three hours for drinking and an additional one hour period for complete bowel evacuation. Another method is to administer PEG 3350, POTASSIUM CHLORIDE, SODIUM BICARBONATE, SODIUM CHLORIDE on the evening before the examination.

Preparation of the solution: PEG 3350, POTASSIUM CHLORIDE, SODIUM BICARBONATE, SODIUM CHLORIDE solution is prepared by filling the container to the 4 liter mark with water and shaking vigorously several times to insure that the ingredients are dissolved. Dissolution is facilitated by using lukewarm water. The solution is more palatable if chilled before administration. However, chilled solution is not recommended for infants. The reconstituted solution should be refrigerated and used within 48 hours. Discard any unused portion.

HOW SUPPLIED

PEG 3350, POTASSIUM CHLORIDE, SODIUM BICARBONATE, SODIUM CHLORIDE with Flavor Pack is supplied in a disposable jug, in powdered form, for oral administration as a solution following reconstitution. Each jug has an attached lemon flavor pack, in powdered form, for the addition of the flavor pack by the pharmacist prior to dispensing.

PEG-3350, SODIUM CHLORIDE, POTASSIUM CHLORIDE, AND SODIUM BICARBONATE FOR ORAL SOLUTION with Flavor Pack: PEG 3350 420 g, sodium bicarbonate 5.72 g, sodium chloride 11.2 g, potassium chloride 1.48 g and lemon flavor pack 2 g (optional). When made up to 4 liters volume with water, the solution contains PEG-3350 31.3 mmol/L, sodium 65 mmol/L, chloride 53 mmol/L, bicarbonate 17 mmol/L and potassium 5 mmol/L.

STORAGE: Store in sealed container at 25°C. When reconstituted, keep solution refrigerated. Use within 48 hours. Discard unused portion.

NDC 40032-050-19

Manufactured by:

Novel Laboratories, Inc.

Somerset, NJ 08873